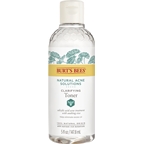 DRUG LABEL: NAS Toner
NDC: 26052-042 | Form: LIQUID
Manufacturer: BURT'S BEES, INC.
Category: otc | Type: HUMAN OTC DRUG LABEL
Date: 20241217

ACTIVE INGREDIENTS: SALICYLIC ACID 1 g/100 1
INACTIVE INGREDIENTS: CITRIC ACID MONOHYDRATE; INULIN; CENTELLA ASIATICA LEAF; CALENDULA OFFICINALIS FLOWER; FRUCTOSE; PENTYLENE GLYCOL; ZINC PIDOLATE; GLYCERIN; SALIX NIGRA BARK; WATER

Natural Acne Solutions Clarifying Toner with Cica 284872.001

ACTIVE INGREDIENT

Salicylic Acid 1.0%

PURPOSE

Acne Treatment

Uses
•For the treatment of acne
•Clear and helps prevent acne blemishes, pimples, blackheads and whiteheads

WARNINGS

For external use only. Skin irritation and dryness is more likely to occur if you use another topical acne medication at the same time. If irritation occurs, only one medication should be used unless directed by a doctor.

KEEP OUT OF REACH OF CHILDREN

If swallowed, get medical help or contact a Poison Control Center right away.

DOSAGE AND ADMINISTRATION

Directions • Clean the skin thoroughly before applying the product • Moisten a cotton pad with toner
and apply to face one to three times daily • Avoid the eye area, if contact occurs rinse thoroughly with water • Because excessive dryness may occur, start with one application daily, then increase to two or three times daily if needed or as directed by a doctor • If bothersome dryness or peeling occurs, reduce application to once a day or every other day

Inactive Ingredients:
water, glycerin, salix nigra (willow) bark extract, centella
asiatica leaf extract, calendula officinalis flower extract,
fructose, citric acid, inulin, pentylene glycol, zinc PCA,
fragrance*

Questions?
800-849-7112 or www.burtsbees.com

PACKAGE LABEL

BURT'S BEES

NATURAL

ACNE

SOLUTIONS

Clarifying

TONER

salicylic acid acne treatment

with soothing cica

5 fl oz / 147.8 mL